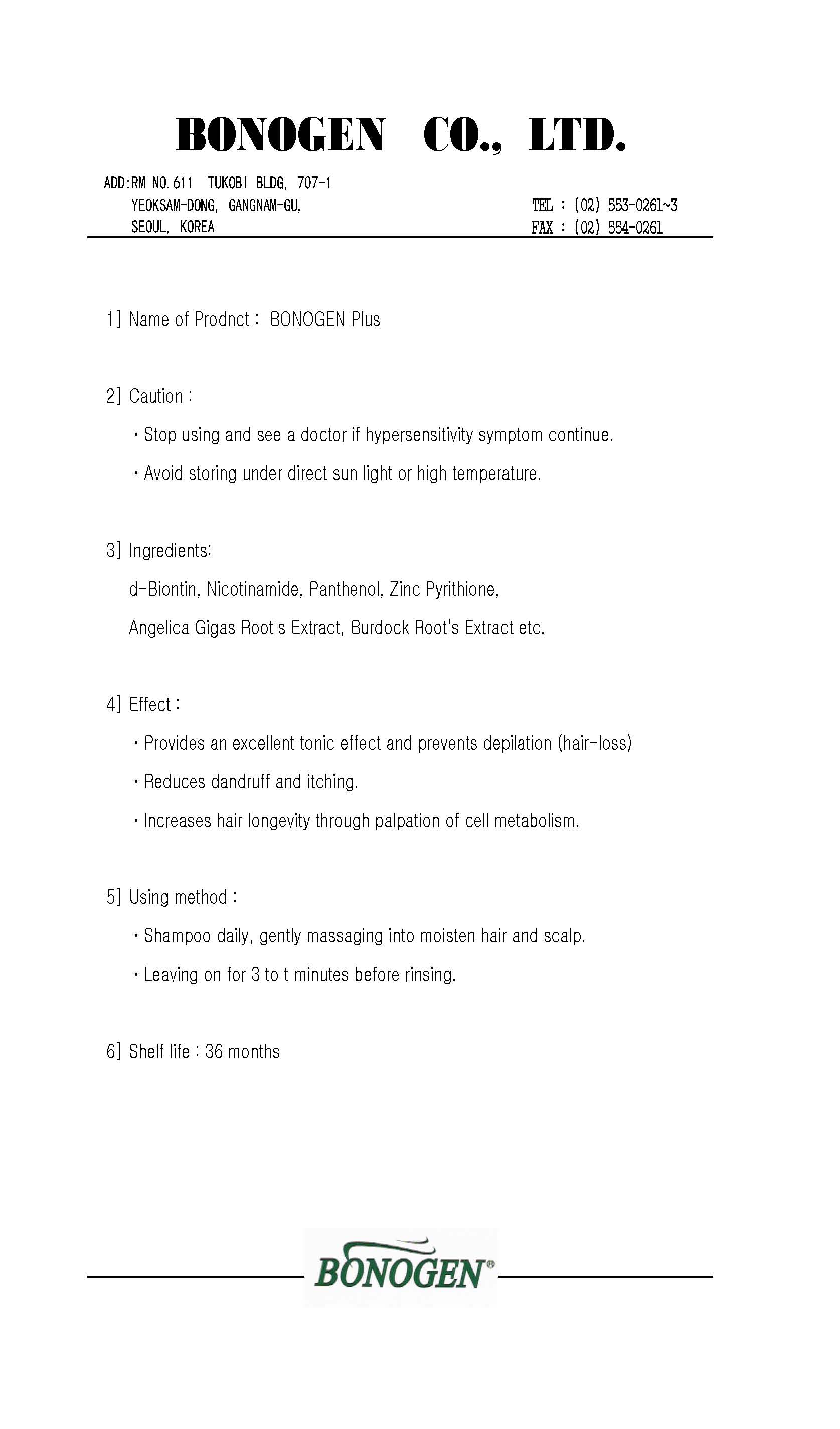 DRUG LABEL: Bonogen Plus
NDC: 50653-2001 | Form: SHAMPOO
Manufacturer: Bonogen Co., Ltd
Category: otc | Type: HUMAN OTC DRUG LABEL
Date: 20100409

ACTIVE INGREDIENTS: PANTHENOL 0.6 g/100 g; BIOTIN 0.06 g/100 g; NADIDE 0.3 g/100 g; PYRITHIONE ZINC 2.1 g/100 g

Drug Facts

ACTIVE INGREDIENT

Active ingredients: d-Biotin, Nicontinamide, Panthenol, Zinc Pyrithione

DESCRIPTION

1) Name of product: Bonogen Plus
2) Caution:
- Stop using and see a doctor if hypersensitivity symptom continue
- Avoid storing under direct sun light or high temperature
3) Effect:
- Provides an excellent tonic effect and prevents depilation (hair-loss)
- Reduces dandruff and itching
- Increases hair longevity through palpation of cell metabilism
4) Using method
- shampoo daily, gently massaging into moisten hair and scalp
- leaving on for 3 to 5 minutes before rinsing
5) Shelf life: 36 months